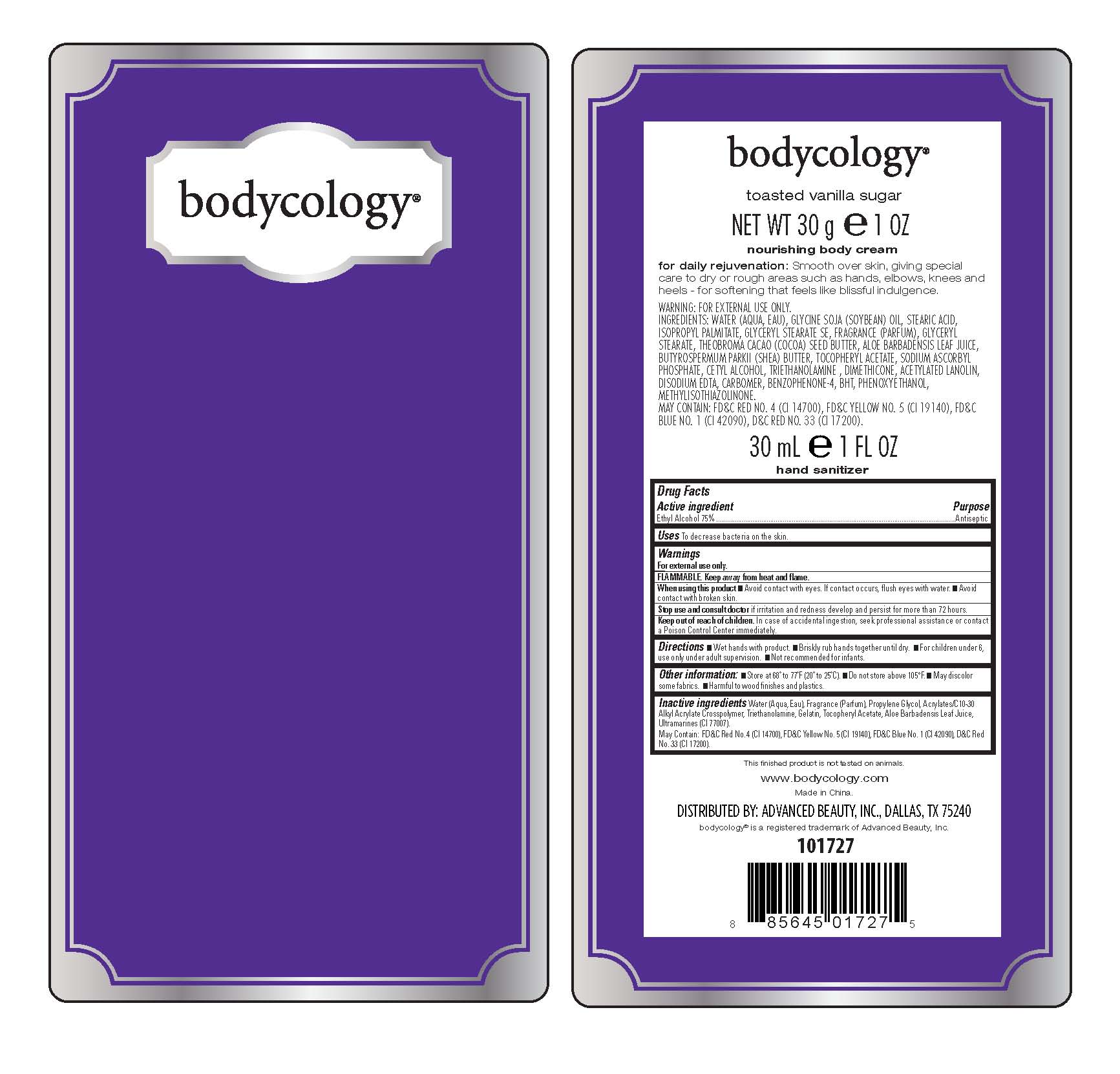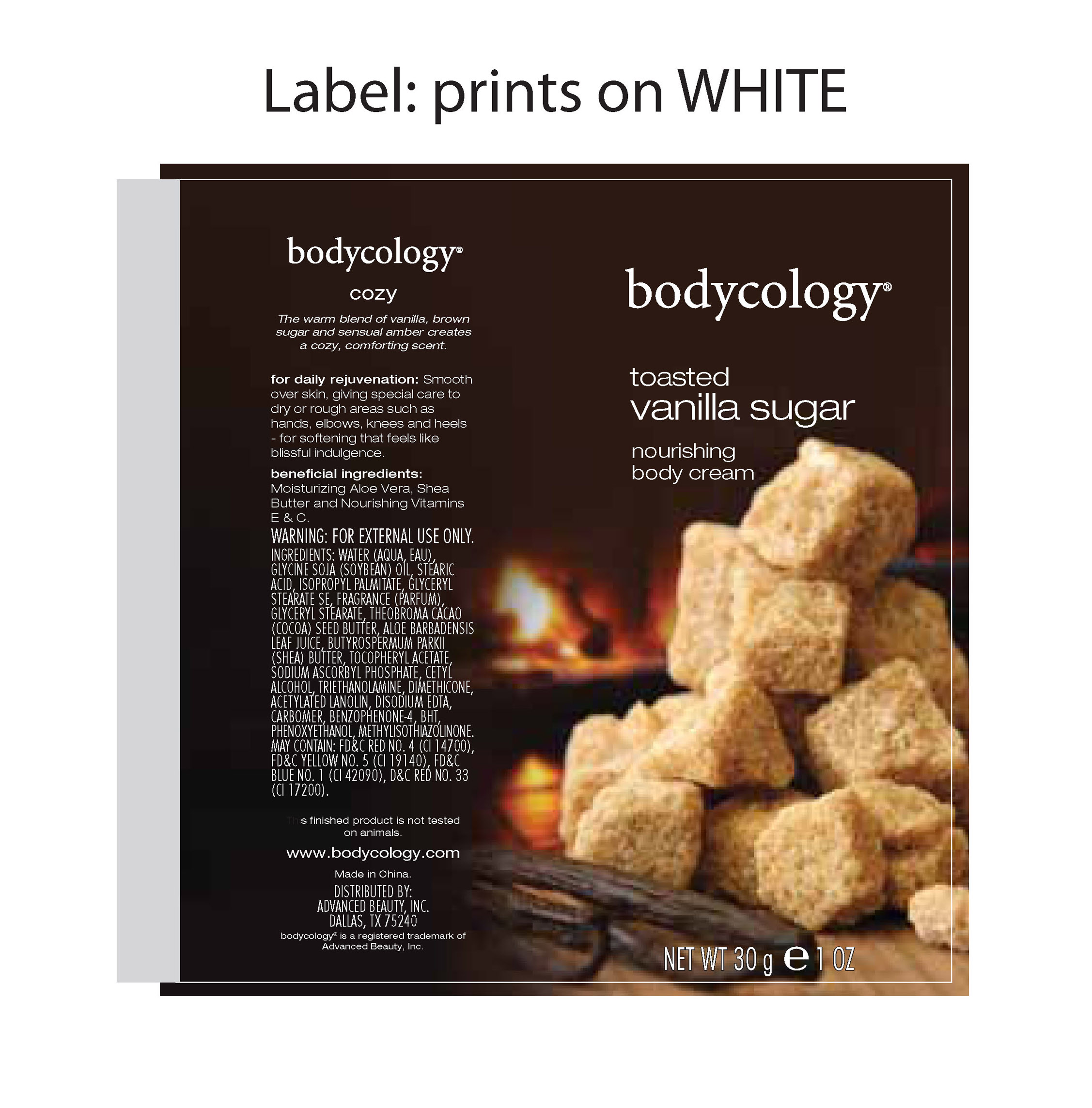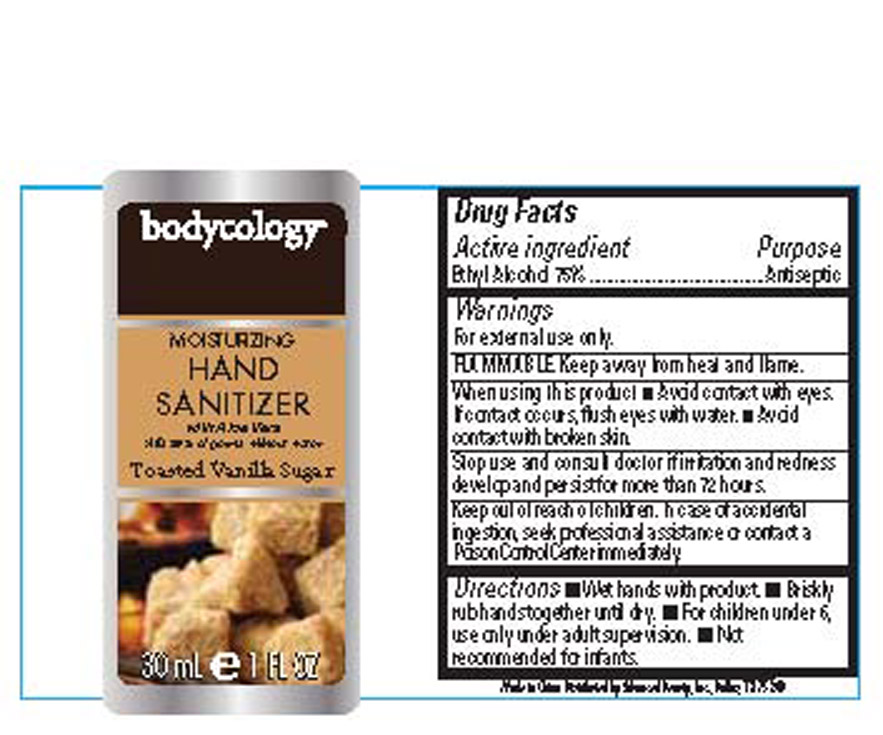 DRUG LABEL: Bodycology
NDC: 51345-057 | Form: KIT | Route: TOPICAL
Manufacturer: Advanced Beauty Systems, Inc.
Category: otc | Type: HUMAN OTC DRUG LABEL
Date: 20120820

ACTIVE INGREDIENTS: ALCOHOL 22.5 mL/30 mL
INACTIVE INGREDIENTS: water; Propylene Glycol; TROLAMINE; GELATIN; .ALPHA.-TOCOPHEROL ACETATE; ALOE VERA LEAF; ULTRAMARINE BLUE; FD&C RED NO. 4; FD&C YELLOW NO. 5; FD&C BLUE NO. 1; D&C RED NO. 33

Bodycology Toasted Vanilla sugar 2 kit

Drug Facts

Active ingredient Purpose

Ethyl Alcohol 75% Antiseptic

PURPOSE

Uses To decrease bacteria on the skin.

Keep out of reach of children. In case of accidental ingestion, seek professional assistance or contact aPoisonControlCenter immediately.

Stop use and consult doctor if irritation and redness develop and persist for more than 72 hours.

Warnings

For external use only.

FLAMMABLE. Keep away from heat and flame.

When using this product

Avoid contact with eyes. If contact occurs, flush eyes with water.

Avoid contact with broken skin.

Directions

-Wet hands with product.

-Briskly rub hands together until dry.

-For children under 6, use only under adult supervision.

-Not recommended for infants.

INACTIVE INGREDIENT

Inactive ingredients: Water (Aqua, Eau), Fragrance (Parfum), Propylene Glycol, Acrylates/C10-30 Alkyl Acrylate Crosspolymer, Triethanolamine, Gelatin, TocopherylAcetate, AloeBarbadensisLeaf Juice, Ultramarines (CI 77007).

May Contain: FD&C Red No. 4 (CI 14700), FD&C Yellow No. 5 (CI 19140), FD&C Blue No. 1 (CI 42090), D&C Red No. 33 (CI 17200).

PACKAGE LABEL

Moisturizing Hand Sanitizer

with Aloe Vera

kills 99% of germs without water

Toasted Vanilla

30 mL 1 Fl Oz